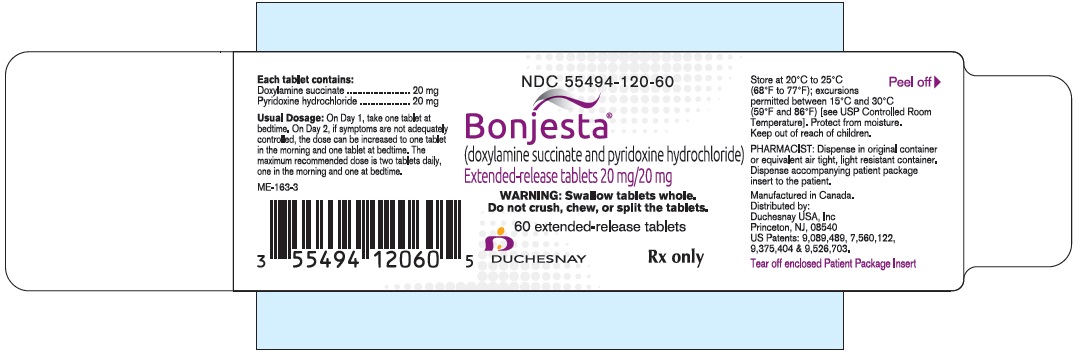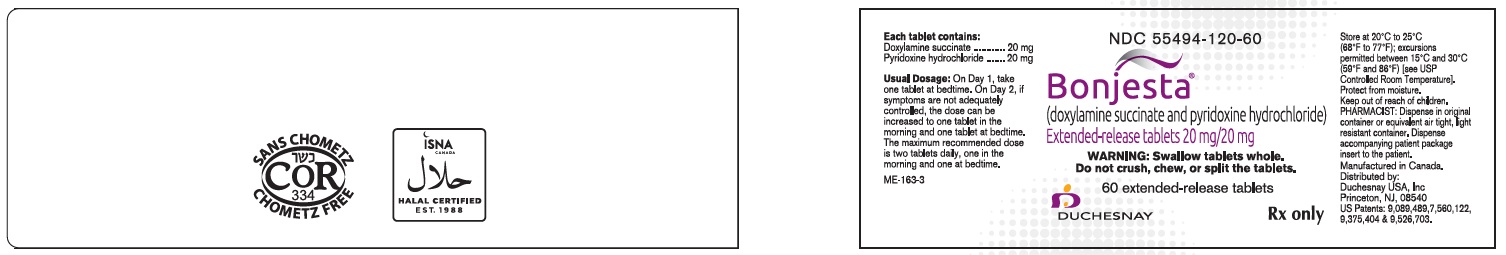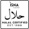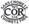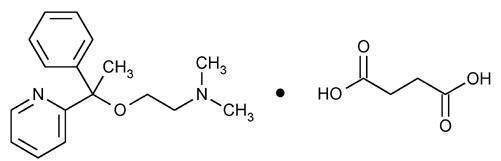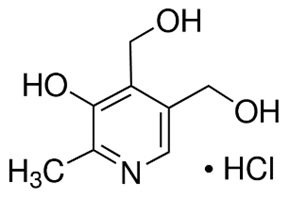 DRUG LABEL: BONJESTA
NDC: 55494-120 | Form: TABLET, EXTENDED RELEASE
Manufacturer: Duchesnay USA, Inc.
Category: prescription | Type: HUMAN PRESCRIPTION DRUG LABEL
Date: 20250225

ACTIVE INGREDIENTS: DOXYLAMINE SUCCINATE 20 mg/1 1; PYRIDOXINE HYDROCHLORIDE 20 mg/1 1
INACTIVE INGREDIENTS: AMMONIA; BUTYL ALCOHOL; CARNAUBA WAX; SILICON DIOXIDE; CROSCARMELLOSE SODIUM; D&C RED NO. 27; ALCOHOL; FERROSOFERRIC OXIDE; FD&C BLUE NO. 2; HYPROMELLOSES; FERRIC OXIDE RED; ISOPROPYL ALCOHOL; MAGNESIUM STEARATE; MAGNESIUM TRISILICATE; METHACRYLIC ACID - ETHYL ACRYLATE COPOLYMER (1:1) TYPE A; CELLULOSE, MICROCRYSTALLINE; POLYETHYLENE GLYCOL 3350; PROPYLENE GLYCOL; SHELLAC; DIMETHICONE; SODIUM BICARBONATE; SODIUM LAURYL SULFATE; TALC; TITANIUM DIOXIDE; TRIETHYL CITRATE

HIGHLIGHTS OF PRESCRIBING INFORMATION

These highlights do not include all the information needed to use BONJESTA safely and effectively. See full prescribing information for BONJESTA.
BONJESTA (doxylamine succinate and pyridoxine hydrochloride), extended-release tablets, for oral use.
Initial U.S. Approval: 1976

RECENT MAJOR CHANGES

Warnings and Precautions, Concomitant Medical Conditions (5.2) 10/2022

1 INDICATIONS AND USAGE

BONJESTA is a fixed dose combination drug product of 20 mg doxylamine succinate, an antihistamine, and 20 mg pyridoxine hydrochloride, a Vitamin B6 analog, indicated for the treatment of nausea and vomiting of pregnancy in women who do not respond to conservative management. (1)

2 DOSAGE AND ADMINISTRATION

On Day 1, take one tablet at bedtime. On Day 2, if symptoms are not adequately controlled, the dose can be increased to one tablet in the morning and one tablet at bedtime. The maximum recommended dose is two tablets daily, one in the morning and one at bedtime, as described in the full prescribing information. (2)

3 DOSAGE FORMS AND STRENGTHS

Extended-release tablets containing 20 mg doxylamine succinate and 20 mg pyridoxine hydrochloride. (3)

4 CONTRAINDICATIONS

- Known hypersensitivity to doxylamine succinate, other ethanolamine derivative antihistamines, pyridoxine hydrochloride or any inactive ingredient in the formulation (4)
- Monoamine oxidase (MAO) inhibitors (4, 7)

5 WARNINGS AND PRECAUTIONS

- Somnolence: BONJESTA may cause somnolence. Avoid engaging in activities requiring complete mental alertness, such as driving or operating heavy machinery, while using BONJESTA until cleared to do so by a healthcare provider (5.1)
- Central nervous system (CNS) depressants: Concurrent use with alcohol or other CNS depressants is not recommended (5.1)
- Anticholinergic actions: Use with caution in patients with increased intraocular pressure, narrow angle glaucoma, stenosing peptic ulcer, pyloroduodenal obstruction and urinary bladder-neck obstruction (5.2)
- Interference with urine drug screen: BONJESTA may interfere with urine screening for methadone, opiates and PCP (5.3)

6 ADVERSE REACTIONS

The most common adverse reaction (≥5 percent and exceeding the rate in placebo) with combination 10 mg doxylamine succinate and 10 mg pyridoxine hydrochloride tablets is somnolence. (6)

To report SUSPECTED ADVERSE REACTIONS, contact Duchesnay Inc. at 1-855-722-7734 or medicalinfo@duchesnayusa.com or FDA at 1-800-FDA-1088 or www.fda.gov/medwatch.

7 DRUG INTERACTIONS

- Severe drowsiness can occur when used in combination with alcohol or other sedating medications. (7)

8 USE IN SPECIFIC POPULATIONS

BONJESTA is intended for use in pregnant women. (8.1)

FULL PRESCRIBING INFORMATION

1 INDICATIONS AND USAGE

BONJESTA is indicated for the treatment of nausea and vomiting of pregnancy in women who do not respond to conservative management.

Limitations of Use

BONJESTA has not been studied in women with hyperemesis gravidarum.

2 DOSAGE AND ADMINISTRATION

2.1 Dosage Information

Initially, take one BONJESTA extended-release tablet orally at bedtime (Day 1). If this dose adequately controls symptoms the next day, continue taking one tablet daily at bedtime only. However, if symptoms persist on Day 2, increase the daily dose to one tablet in the morning and one tablet at bedtime. The maximum recommended dose is two tablets per day, one in the morning and one at bedtime.

Take on an empty stomach with a glass of water [see Clinical Pharmacology (12.3)]. Swallow tablets whole. Do not crush, chew, or split BONJESTA tablets.

Take daily and not on an as needed basis. Reassess the woman for continued need for BONJESTA as her pregnancy progresses.

3 DOSAGE FORMS AND STRENGTHS

BONJESTA extended-release tablets are pink, round, film coated tablets containing 20 mg doxylamine succinate and 20 mg pyridoxine hydrochloride, imprinted on one side with the pink image of a pregnant woman and a "D" on the other side.

4 CONTRAINDICATIONS

BONJESTA is contraindicated in women with any of the following conditions:

- Known hypersensitivity to doxylamine succinate, other ethanolamine derivative antihistamines, pyridoxine hydrochloride or any inactive ingredient in the formulation
- Monoamine oxidase (MAO) inhibitors intensify and prolong the adverse central nervous system effects of BONJESTA [see Drug Interactions (7.1)].

5 WARNINGS AND PRECAUTIONS

5.1 Somnolence and Severe Drowsiness

BONJESTA may cause somnolence due to the anticholinergic properties of doxylamine succinate, an antihistamine. Women should avoid engaging in activities requiring complete mental alertness, such as driving or operating heavy machinery, while using BONJESTA until cleared to do so by their healthcare provider.

BONJESTA use is not recommended if a woman is concurrently using central nervous system (CNS) depressants including alcohol. The combination may result in severe drowsiness leading to falls or accidents [see Drug Interactions (7.1)].

5.2 Concomitant Medical Conditions

BONJESTA has anticholinergic properties and, therefore, should be used with caution in women with: increased intraocular pressure, narrow angle glaucoma, stenosing peptic ulcer, pyloroduodenal obstruction or urinary bladder-neck obstruction.

5.3 Interference with Urine Screen for Methadone, Opiates and Phencyclidine Phosphate (PCP)

There have been reports of false positive urine screening tests for methadone, opiates, and PCP with doxylamine succinate/pyridoxine hydrochloride use [see Drug Interactions (7.3)].

6 ADVERSE REACTIONS

- The following adverse reactions are discussed elsewhere in the labeling:
- Somnolence [see Warnings and Precautions (5.1)]
- Falls or other accidents resulting from the effect of the combined use of BONJESTA with CNS depressants including alcohol [see Warnings and Precautions (5.1)]

6.1 Clinical Trial Experience

Because clinical trials are conducted under widely varying conditions, adverse reaction rates observed in the clinical trials of a drug cannot be directly compared to rates in the clinical trials of another drug and may not reflect the rates observed in clinical practice.

The safety and efficacy of combination 10 mg doxylamine succinate and 10 mg pyridoxine hydrochloride tablets compared to placebo was studied in a double-blind, randomized, multi-center trial in 261 women with nausea and vomiting of pregnancy. The mean gestational age at enrollment was 9.3 weeks, range 7 to 14 weeks gestation [see Clinical Studies (14)]. Adverse reactions that occurred at an incidence ≥5 percent and exceeded the incidence for placebo are summarized in Table 1.

Table 1: Number (Percent) of Women with ≥ 5 Percent Adverse Reactions in a 15-Day Placebo-Controlled Trial of Combination 10 mg Doxylamine Succinate and 10 mg Pyridoxine Hydrochloride Tablets (Only Those Adverse Reactions Occurring at an Incidence ≥ 5 Percent and at a Higher Incidence than Placebo are Shown)

Adverse Reaction | Combination 10 mg Doxylamine Succinate and 10 mg Pyridoxine Hydrochloride Tablets; (N = 133) | Placebo; (n = 128)
Somnolence | 19 (14.3%) | 15 (11.7%)

6.2 Postmarketing Experience

The following adverse events, listed alphabetically, have been identified during post-approval use of the combination of 10 mg doxylamine succinate and 10 mg pyridoxine hydrochloride. Because these reactions are reported voluntarily from a population of uncertain size, it is not always possible to reliably estimate their frequency or establish a causal relationship to drug exposure.

Cardiac disorders: dyspnea, palpitation, tachycardia

Ear and labyrinth disorders: vertigo

Eye disorders: vision blurred, visual disturbances

Gastrointestinal disorders: abdominal distension, abdominal pain, constipation, diarrhea

General disorders and administration site conditions: chest discomfort, fatigue, irritability, malaise

Immune system disorders: hypersensitivity

Nervous system disorders: dizziness, headache, migraines, paresthesia, psychomotor hyperactivity

Psychiatric disorders: anxiety, disorientation, insomnia, nightmares

Renal and urinary disorders: dysuria, urinary retention

Skin and subcutaneous tissue disorders: hyperhidrosis, pruritus, rash, rash maculopapular

7 DRUG INTERACTIONS

7.1 Drug Interactions

Use of BONJESTA is contraindicated in women who are taking monoamine oxidase inhibitors (MAOIs), which prolong and intensify the adverse central nervous system effects (the anticholinergic effects) of antihistamines. Concurrent use of alcohol and other CNS depressants (such as hypnotic sedatives and tranquilizers) with BONJESTA is not recommended.

7.2 Drug-Food Interactions

A food-effect trial demonstrated that the delay in the onset of action of BONJESTA may be further delayed, and a reduction in absorption may occur when tablets are taken with food [see Dosage and Administration (2), Clinical Pharmacology (12.3)]. Therefore, BONJESTA should be taken on an empty stomach with a glass of water [see Dosage and Administration (2)].

7.3 False Positive Urine Tests for Methadone, Opiates and PCP

False positive drug screens for methadone, opiates, and PCP can occur with doxylamine succinate/pyridoxine hydrochloride use. Confirmatory tests, such as Gas Chromatography Mass Spectrometry (GC-MS), should be used to confirm the identity of the substance in the event of a positive immunoassay result.

8 USE IN SPECIFIC POPULATIONS

8.1 Pregnancy

Risk Summary

BONJESTA is intended for the treatment of nausea and vomiting of pregnancy in women who do not respond to conservative management. Maternal risks are discussed throughout the labeling. No increased risk for congenital malformations has been reported in epidemiologic studies in pregnant women.

In the U.S. general population, the estimated background risks for major birth defects and miscarriage in clinically recognized pregnancies are 2-4% and 15-20%, respectively.

Data

Human Data

The combination of doxylamine succinate and pyridoxine hydrochloride has been the subject of many epidemiological studies (cohort, case control and meta-analyses) designed to detect possible teratogenicity. A meta-analysis of 16 cohort and 11 case-control studies published between 1963 and 1991 reported no increased risk for malformations from first trimester exposures to doxylamine succinate and pyridoxine hydrochloride, with or without dicyclomine hydrochloride. A second meta-analysis of 12 cohort and 5 case-control studies published between 1963 and 1985 reported no statistically significant relationships between fetal abnormalities and the first trimester use of the combination of doxylamine succinate and pyridoxine hydrochloride with or without dicyclomine hydrochloride.

8.2 Lactation

Risk Summary

Women should not breastfeed while using BONJESTA.

The molecular weight of doxylamine succinate is low enough that passage into breast milk can be expected. Excitement, irritability and sedation have been reported in nursing infants presumably exposed to doxylamine succinate through breast milk. Infants with apnea or other respiratory syndromes may be particularly vulnerable to the sedative effects of BONJESTA resulting in worsening of their apnea or respiratory conditions.

Pyridoxine hydrochloride is excreted into breast milk. There have been no reports of adverse events in infants presumably exposed to pyridoxine hydrochloride through breast milk.

8.4 Pediatric Use

The safety and effectiveness of BONJESTA in children under 18 years of age have not been established.

Fatalities have been reported from doxylamine overdose in children. The overdose cases have been characterized by coma, grand mal seizures and cardiorespiratory arrest. Children appear to be at a high risk for cardiorespiratory arrest. A toxic dose for children of more than 1.8 mg/kg has been reported. A 3 year old child died 18 hours after ingesting 1,000 mg doxylamine succinate. However, there is no correlation between the amount of doxylamine ingested, the doxylamine plasma level and clinical symptomatology.

10 OVERDOSAGE

10.1 Signs and Symptoms of Overdose

BONJESTA is an extended-release formulation, therefore, signs and symptoms of intoxication may not be apparent immediately.

Signs and symptoms of overdose may include restlessness, dryness of mouth, dilated pupils, sleepiness, vertigo, mental confusion and tachycardia.

At toxic doses, doxylamine exhibits anticholinergic effects, including seizures, rhabdomyolysis, acute renal failure and death.

10.2 Management of Overdose

If treatment is needed, it consists of gastric lavage or activated charcoal, whole bowel irrigation and symptomatic treatment. For additional information about overdose treatment, call a poison control center (1-800-222-1222).

11 DESCRIPTION

BONJESTA extended-release tablets consist of an enteric-coated core containing 10 mg doxylamine succinate and 10 mg pyridoxine hydrochloride, and an immediate release coating of 10 mg doxylamine succinate and 10 mg pyridoxine hydrochloride.

BONJESTA tablets are round, pink, film-coated, multilayer, extended-release tablets containing a total of 20 mg doxylamine succinate and 20 mg pyridoxine hydrochloride. Tablets are imprinted on one side with the pink image of a pregnant woman and a “D” on the other side.

Inactive ingredients are as follows: ammonium hydroxide, n-butanol, carnauba wax powder, colloidal silicon dioxide, croscarmellose sodium, D&C Red#27 aluminum lake, denatured alcohol, ferrosoferric oxide, FD&C Blue #2 aluminum lake, hypromellose, iron oxide red, isopropyl alcohol, magnesium stearate, magnesium trisilicate, methacrylic acid copolymer, microcrystalline cellulose 102, PEG 3350, propylene glycol, shellac glaze, simethicone, sodium bicarbonate, sodium lauryl sulfate, talc, titanium dioxide, triethyl citrate.

BONJESTA is certified Kosher, Kosher for Passover and Halal .

Doxylamine Succinate

Doxylamine succinate is classified as an antihistamine. The chemical name for doxylamine succinate is ethanamine, N,N-dimethyl-2-[1-phenyl-1-(2-pyridinyl)ethoxy]-, butanedioate (1:1). The empirical formula is C17H22N2O • C4H6O4 and the molecular mass is 388.46. The structural formula is:

Doxylamine succinate is a white to creamy white powder that is very soluble in water and alcohol, freely soluble in chloroform and very slightly soluble in ether and benzene.

Pyridoxine Hydrochloride

Pyridoxine hydrochloride is a vitamin B6 analog. The chemical name for pyridoxine hydrochloride is 3,4-pyridinedimethanol, 5-hydroxy-6-methyl-, hydrochloride. The empirical formula is C8H11NO3 • HCl and the molecular mass is 205.64. The structural formula is:

Pyridoxine hydrochloride is a white or practically white crystalline powder that is freely soluble in water, slightly soluble in alcohol and insoluble in ether.

12 CLINICAL PHARMACOLOGY

12.1 Mechanism of Action

The mechanism of action of BONJESTA is unknown.

12.3 Pharmacokinetics

The pharmacokinetics of BONJESTA has been characterized in healthy non-pregnant adult women.

Absorption

In a single-dose, crossover clinical trial conducted in 48 healthy, premenopausal women under fasting conditions, one BONJESTA (20 mg doxylamine succinate and 20 mg pyridoxine) tablet was bioequivalent to two combination tablets of 10 mg doxylamine succinate and 10 mg pyridoxine hydrochloride based on the exposure (AUC) and peak concentration (Cmax) of doxylamine and baseline corrected pyridoxal 5′-phosphate. Mean ± SD plasma (whole blood for pyridoxal) pharmacokinetic (PK) parameters are summarized in Table 2.

Table 2 – Mean ± SD Single-Dose Pharmacokinetics of BONJESTA in Healthy Premenopausal Adult Women
 |  | BONJESTA Mean±SD
 |  | AUC0-t (ng•h/mL) | AUC0-inf (ng•h/mL) | AUC0-72 (ng•h/mL) | Cmax (ng/mL) | Tmax [Median (range)] (h)
Doxylamine | N=48 | 1367.0 ± 356.7 | 1425.8 ± 405.1 | --- | 92.3 ± 15.7 | 4.5 (2.5-5.5)
Pyridoxine | N=47 | 42.3 ± 14.7 | 42.5 ± 14.7 | --- | 47.1 ± 18.7 | 0.5 (0.5-4.7)
Pyridoxal [Baseline corrected values] | N=48 [N=46 for AUC0-inf] | 203.7 ± 51.7 | 233.6 ± 55.9 | --- | 58.9 ± 17.0 | 3.0 (0.8-5.0)
Pyridoxal 5′-Phosphate | N=48 | --- | --- | 1076.2 ± 382.2 | 30.1 ± 9.2 | 9.0 (3.0-16.0)

In a multiple-dose, crossover clinical trial conducted in 31 healthy, premenopausal women, one BONJESTA (20 mg doxylamine succinate and 20 mg pyridoxine) tablet given twice daily for 11 days was bioequivalent to one combination tablet of 10 mg doxylamine succinate and 10 mg pyridoxine hydrochloride given three times daily (1 tablet in the morning, 1 tablet in the afternoon and 2 tablets at bedtime), based on the exposure (AUC) and peak concentration (Cmax) of doxylamine and baseline corrected pyridoxal 5′-phosphate. Mean ± SD plasma (whole blood for pyridoxal) PK parameters are summarized in Table 3.

Table 3 – Mean ± SD Multiple-Dose (Day 11) Pharmacokinetic Parameters of BONJESTA (given twice daily) in Healthy Premenopausal Adult Women
 |  | BONJESTA Mean±SD
 |  | AUC0-24 (ng•h/mL) | AUC0-12 (ng•h/mL) | AUC0-6 (ng•h/mL) | Cmax (ng/mL) | Tmax [Median (range)] (h)
Doxylamine | N=34 | 2879.4 ± 696.0 | 1573.2 ± 406.5 | 883.6 ± 228.5 | 173.6 ± 45.5 | 3.5 (1.0-20.0)
Pyridoxine | N=34 | 80.0 ± 22.7 | 46.3 ± 15.4 | 45.3 ± 16.3 | 48.2 ± 23.7 | 1.5 (0.3-16.5)
Pyridoxal [Baseline corrected values] | N=34 | 1511.3 ± 300.0 | 848.1 ± 183.6 | 647.2 ± 149.6 | 189.6 ± 48.3 | 3.0 (2.0-15.0)
Pyridoxal 5′-Phosphate | N=34 | 1742.3 ± 554.3 | 831.7 ± 274.5 | 426.2 ± 144.0 | 85.9 ± 26.2 | 15.0 (2.0-24.0)

Food Effect

In a single-dose, crossover clinical trial conducted in 23 healthy, premenopausal women, the administration of a high fat, high calorie meal delayed the absorption of doxylamine, pyridoxine, and pyridoxine metabolites. This delay is associated with lower peak concentrations of doxylamine, pyridoxine, and pyridoxal. The extent of absorption for pyridoxine was decreased.

The effect of food on the peak concentration and the extent of absorption of the pyridoxine component is more complex because the pyridoxine metabolites such as pyridoxal, pyridoxamine, pyridoxal 5′-phosphate, and pyridoxamine 5′-phosphate also contribute to the biological activity. Food significantly reduces the bioavailability of pyridoxine, lowering its Cmax and AUC by approximately 67% and 37%, respectively, compared to fasting conditions. Similarly, food significantly reduces pyridoxal Cmax by approximately 46% compared to fasting conditions. In contrast, food did not affect pyridoxal 5′-phosphate Cmax and AUC.

Table 4 – Mean ± SD Pharmacokinetic Parameters of Doxylamine and Pyridoxine Metabolites Following a Single Dose Administration of BONJESTA Under Fed and Fasted Conditions in Healthy Premenopausal Adult Women
 |  | BONJESTA N=23
 |  | AUC0-t (ng•h/mL) | AUC0-inf (ng•h/mL) | Cmax (ng/mL) | Tmax [Profile of Subject 20 was excluded] , [Median (range)] (h) | T1/2el (h)
Doxylamine Mean±SD | Fasted | 1273.7 ± 276.2 | 1321.9 ± 315.5 | 85.9 ± 10.6 | 3.5 (2.5-5.5) | 11.9 ± 2.2
Doxylamine Mean±SD | Fed | 1242.8 ± 254.0 | 1281.4 ± 282.9 | 64.5 ± 15.2 | 6.5 (2.0-24.0) | 12.7 ± 2.60
Pyridoxine Mean±SD | Fasted | 34.7 ± 10.6 | 35.1 ± 8.5 | 38.9 ± 19.3 | 0.8 (0.3-4.3) | 0.4 ± 0.2
Pyridoxine Mean±SD | Fed | 22.8 ± 9.9 | 27.0 ± 10.1 | 12.7 ± 5.7 | 8.0 (1.0-21.0) | 1.2 ± 2.4
Pyridoxal [Baseline corrected values] Mean±SD | Fasted | 209.4 ± 30.0 | 244.0 ± 32.5 | 62.0 ± 17.8 | 2.3 (0.8-5.0) | 8.0 ± 1.7
Pyridoxal [Baseline corrected values] Mean±SD | Fed | 204.2 ± 25.7 | 249.2 ± 43.0 | 33.1 ± 6.1 | 6.0 (1.0-21.0) | 12.5 ± 7.6
Pyridoxal 5′-phosphate Mean±SD | Fasted | 1021.7 ± 318.5 | --- | 27.4 ± 7.7 | 5.0 (3.0-71.8) | ---
Pyridoxal 5′-phosphate Mean±SD | Fed | 1064.6 ± 386.9 | --- | 30.2 ± 10.0 | 16.0 (6.0-22.0) | ---

Distribution

Pyridoxine is highly protein bound, primarily to albumin. Its main active metabolite, pyridoxal 5′-phosphate (PLP) accounts for at least 60% of circulating vitamin B6 concentrations.

Metabolism

Doxylamine is biotransformed in the liver by N-dealkylation to its principal metabolites N-desmethyl-doxylamine and N, N-didesmethyldoxylamine.

Pyridoxine is a prodrug primarily metabolized in the liver.

Excretion

The principal metabolites of doxylamine, N-desmethyl-doxylamine and N, N-didesmethyldoxylamine, are excreted by the kidney.

The terminal elimination half-life of doxylamine and pyridoxine are 11.9 hours and 0.4 hours, respectively (see Table 5).

Table 5 – Terminal Elimination Half-Life (T1/2el) for BONJESTA Administered as a Single Dose under Fasting Conditions in Healthy Premenopausal Adult Women (N=23)
 | BONJESTA T1/2el (h)
Doxylamine | 11.9 ± 2.2
Pyridoxine | 0.4 ± 0.2 [N=12]
Pyridoxal | 8.0 ± 1.7 [Baseline corrected value]

Use in Specific Populations

Race: No pharmacokinetic studies have been conducted related to race.

Hepatic Impairment: No pharmacokinetic studies have been conducted in hepatic impaired patients.

Renal Impairment: No pharmacokinetic studies have been conducted in renal impaired patients.

13 NONCLINICAL TOXICOLOGY

13.1 Carcinogenesis, Mutagenesis and Impairment of Fertility

Carcinogenicity

Two-year carcinogenicity studies in rats and mice have been conducted with doxylamine succinate. Doxylamine succinate is not likely to have human carcinogenic potential. The carcinogenic potential of pyridoxine hydrochloride has not been evaluated.

14 CLINICAL STUDIES

There have been no efficacy and safety trials conducted with BONJESTA.

A double-blind, randomized, multi-center, placebo-controlled study was conducted to support the safety and efficacy of 10 mg doxylamine succinate and 10 mg pyridoxine hydrochloride tablets (a different formulation and dosage strength than BONJESTA) in the treatment of nausea and vomiting of pregnancy. Adult women 18 years of age or older and 7 to 14 weeks gestation (median 9 weeks of gestation) with nausea and vomiting of pregnancy were randomized to 14 days of 10 mg doxylamine succinate and 10 mg pyridoxine hydrochloride tablets or placebo. Two tablets of 10 mg doxylamine succinate and 10 mg pyridoxine hydrochloride were administered at bedtime on Day 1. If symptoms of nausea and vomiting persisted into the afternoon hours of Day 2, the woman was directed to take her usual dose of two tablets at bedtime that night and, beginning on Day 3, to take one tablet in the morning and two tablets at bedtime. Based upon assessment of remaining symptoms at her clinic visit on Day 4 (± 1 day), the woman may have been directed to take an additional tablet mid-afternoon. A maximum of four tablets (one in the morning, one in the mid-afternoon and two at bedtime) were taken daily.

Over the treatment period, 19% of 10 mg doxylamine succinate and 10 mg pyridoxine hydrochloride tablet-treated women remained on 2 tablets daily, 21% received 3 tablets daily, and 60% received 4 tablets daily.

The primary efficacy endpoint was the change from baseline at Day 15 in the Pregnancy Unique-Quantification of Emesis (PUQE) score. The PUQE score incorporates the number of daily vomiting episodes, number of daily heaves, and length of daily nausea in hours, for an overall score of symptoms rated from 3 (no symptoms) to 15 (most severe).

At baseline, the mean PUQE score was 9.0 in the 10 mg doxylamine succinate and 10 mg pyridoxine hydrochloride tablets arm and 8.8 in the placebo arm. There was a 0.7 (95% confidence interval 0.2 to 1.2 with p-value 0.006) mean decrease (improvement in nausea and vomiting symptoms) from baseline in PUQE score at Day 15 with 10 mg doxylamine succinate and 10 mg pyridoxine hydrochloride tablets compared to placebo (see Table 6).

Table 6 – Change from Baseline in the Primary Endpoint, Pregnancy Unique-Quantification of Emesis (PUQE) Score at Day 15. (Intent-to-Treat Population with Last-Observation Carried Forward)
PUQE Score [The Pregnancy-Unique Quantification of Emesis and Nausea (PUQE) score incorporated the number of daily vomiting episodes, number of daily heaves, and length of daily nausea in hours, for an overall score of symptoms rated from 3 (no symptoms) to 15 (most severe). Baseline was defined as the PUQE score completed at the enrollment visit.] | Combination 10 mg Doxylamine Succinate and 10 mg Pyridoxine Hydrochloride Tablets; N=131 | Placebo; N=125 | Treatment Difference [95% Confidence Interval]
Baseline Change from baseline at Day 15 | 9.0 ± 2.1 -4.8 ± 2.7 | 8.8 ± 2.1 -3.9 ± 2.6 | -0.7 [-1.2, -0.2]

16 HOW SUPPLIED/STORAGE AND HANDLING

16.1 How supplied

BONJESTA extended-release tablets are supplied in a high-density polyethylene bottle with a polypropylene child-resistant cap and a silica gel desiccant canister. Each pink, round, film-coated, extended-release tablet contains 20 mg doxylamine succinate and 20 mg pyridoxine hydrochloride, and is imprinted on one side with the pink image of a pregnant woman and a "D" on the other side. BONJESTA tablets are provided as follows:

NDC 55494-120-60 Bottles of 60
NDC 55494-120-10 Bottles of 100

16.2 Storage and Handling

Store at 20°C to 25°C (68°F to 77°F); excursions permitted between 15°C and 30°C (59°F and 86°F) [see USP Controlled Room Temperature]. Keep bottle tightly closed and protect from moisture. Do not remove desiccant canister from bottle.

17 PATIENT COUNSELING INFORMATION

See FDA-approved patient labeling (Patient Information)

Somnolence

Inform women to avoid engaging in activities requiring complete mental alertness, such as driving or operating heavy machinery, while using BONJESTA until cleared to do so.

Inform women of the importance of not taking BONJESTA with alcohol or sedating medications, including other antihistamines (present in some cough and cold medications), opiates and sleep aids because somnolence could worsen leading to falls or other accidents.

Interference with urine drug screening

Inform women that use of BONJESTA may result in false positive urine drug screening for methadone, opiates and PCP.

BONJESTA is a registered trademark of Duchesnay Inc.

U.S. Patent Nos. 9,089,489, 7,560,122, 9,375,404 & 9,526,703.

Manufactured by:
Duchesnay Inc.
950 boul. Michèle-Bohec
Blainville, Québec
Canada J7C 5E2

Distributed by:
Duchesnay USA, Inc.
Princeton, NJ 08540
Tel: 1-855-722-7734
Fax: 1-888-588-8508
www.duchesnayusa.com

©2018, Duchesnay Inc. All rights reserved.

Patient Package Insert

Patient Information

BONJESTA (bonn jest ah)

(doxylamine succinate and pyridoxine hydrochloride)

extended-release tablets, for oral use

What is BONJESTA?

- BONJESTA is a prescription medicine used to treat nausea and vomiting of pregnancy in women who have not improved with change in diet or other non-medicine treatments.
- It is not known if BONJESTA is safe and effective in women with severe nausea and vomiting of pregnancy, a condition called hyperemesis gravidarum. Women with this condition may need to be hospitalized.
- It is not known if BONJESTA is safe and effective in children under 18 years of age.

Do not take BONJESTA if you:

- are allergic to doxylamine succinate, other ethanolamine derivative antihistamines, pyridoxine hydrochloride or any of the ingredients in BONJESTA. See the end of this Patient Information leaflet for a complete list of ingredients in BONJESTA.
- take monoamine oxidase inhibitors (MAOIs). Ask your healthcare provider or pharmacist if you are not sure if you take an MAOI, including Marplan, Nardil, Emsam, Eldepryl, Zelapar, and Parnate.

Before taking BONJESTA, tell your healthcare provider about all of your medical conditions, including if you:

- have eye problems called increased intraocular pressure or narrow angle glaucoma.
- have a stomach problem called stenosing peptic ulcer or pyloroduodenal obstruction.
- have a bladder problem called urinary bladder-neck obstruction.
- are breastfeeding or plan to breastfeed. BONJESTA can pass into your breast milk and may harm your baby. You should not breastfeed while using BONJESTA.

Tell your healthcare provider about all the medicines you take, including prescription and over-the-counter medicines, vitamins, and herbal supplements.

How should I take BONJESTA?

- Talk to your healthcare provider about how much BONJESTA to take and when to take it.
- Take BONJESTA everyday as prescribed by your healthcare provider. Do not stop taking BONJESTA without talking to your healthcare provider first.
- See the following schedule for the right way you should start taking BONJESTA:
  - Start with 1 tablet by mouth at bedtime. If your nausea and vomiting is better or controlled on Day 2, continue to take 1 tablet each day at bedtime.
  - If you still have nausea and vomiting on Day 2, start taking 1 tablet in the morning and 1 tablet at bedtime each day.
- Do not take more than 2 tablets (1 in the morning and 1 at bedtime) each day.
- Take BONJESTA on an empty stomach with a glass of water.
- Take BONJESTA tablets whole. Do not crush, chew, or break BONJESTA tablets before swallowing. If you cannot swallow BONJESTA tablets whole, tell your healthcare provider.
  - If you take too much BONJESTA (overdose), you may have the following symptoms: restlessness, dry mouth, the pupils of your eyes become larger (dilated), sleepiness, dizziness, confusion, fast heart rate, seizures, muscle pain or weakness, urination changes and build-up of fluid in the body. If you have these symptoms and they are severe, they may lead to death. If you take too much BONJESTA, call your poison control center at 1-800-222-1222.

What are the possible side effects of BONJESTA?

BONJESTA may cause serious side effects, including drowsiness.

Drowsiness is a common side effect when taking BONJESTA, but can also be severe:

- Do not drive, operate heavy machinery, or do other activities that need your full attention unless your healthcare provider says that you may do so.
- Do not drink alcohol, or take other central nervous system depressants such as cough and cold medicines, certain pain medicines, and medicines that help you sleep while you take BONJESTA. Severe drowsiness can happen or become worse causing falls or accidents.

BONJESTA may cause false positive urine drug screening test for methadone, opiates and PCP.

These are not all the possible side effects of BONJESTA.

Call your doctor for medical advice about side effects. You may report side effects to FDA at 1-800-FDA-1088.

How should I store BONJESTA?

- Store BONJESTA at room temperature between 68°F to 77°F (20°C to 25°C).
- Keep the bottle tightly closed to protect BONJESTA from moisture.
- The BONJESTA bottle contains a desiccant canister to help keep your medicine dry. Do not throw away the desiccant.
- Safely throw away medicine that is past the expiration date or no longer needed.

Keep BONJESTA and all medicines out of the reach of children.

General information about the safe and effective use of BONJESTA.

Medicines are sometimes prescribed for purposes other than those listed in a Patient Information leaflet. You can ask your pharmacist or healthcare provider for information about BONJESTA that is written for health professionals. Do not use BONJESTA for a condition for which it was not prescribed. Do not give BONJESTA to other people, even if they have the same symptoms that you have. It may harm them.

What are the ingredients in BONJESTA?

Active ingredient: doxylamine succinate (an antihistamine) and pyridoxine hydrochloride (vitamin B6).

Inactive ingredients: ammonium hydroxide, n-butanol, carnauba wax powder, colloidal silicon dioxide, croscarmellose sodium, D&C Red#27 aluminum lake, denatured alcohol, ferrosoferric oxide, FD&C Blue #2 aluminum lake, hypromellose, iron oxide red, isopropyl alcohol, magnesium stearate, magnesium trisilicate, methacrylic acid copolymer, microcrystalline cellulose 102, PEG 3350, propylene glycol, shellac glaze, simethicone, sodium bicarbonate, sodium lauryl sulfate, talc, titanium dioxide, triethyl citrate.

Distributed by: Duchesnay USA, Inc., Princeton, NJ, 08540
For more information, go to www.duchesnayusa.com or call 1-855-722-7734.

This Patient Information has been approved by the U.S. Food and Drug Administration Issued: 10/2022

Package/Label Display Panel

Bottle Label-Outside Front Cover with Imprint Area for Lot & Expiry

NDC 55494-120-60

Bonjesta®
(doxylamine succinate and pyridoxine hydrochloride)
Extended-release tablets 20mg/20mg

WARNING: Swallow tablets whole.
Do not crush, chew, or split the tablets.

60 extended-release tablets

DUCHESNAY

Rx only

Bottle Label – Inside Cover